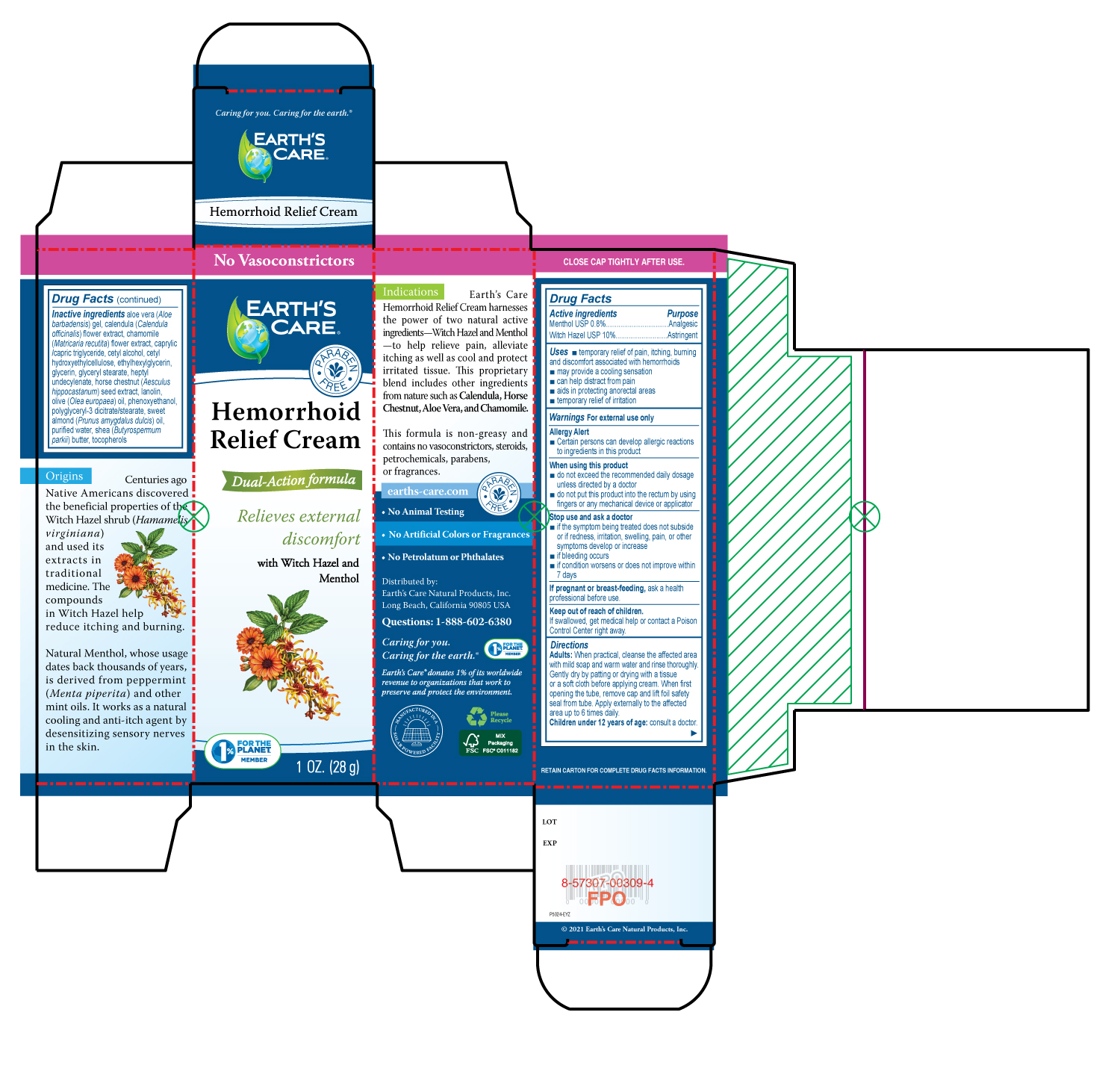 DRUG LABEL: Earths Care Hemorrhoid Relief
NDC: 24286-1570 | Form: CREAM
Manufacturer: DLC Laboratories, Inc.
Category: otc | Type: HUMAN OTC DRUG LABEL
Date: 20260107

ACTIVE INGREDIENTS: WITCH HAZEL 10 g/100 g; MENTHOL, UNSPECIFIED FORM 0.8 g/100 g
INACTIVE INGREDIENTS: WATER; LANOLIN; ALOE VERA LEAF; CETYL HYDROXYETHYLCELLULOSE (350000 MW); GLYCERIN; SHEA BUTTER; ALMOND OIL; GLYCERYL MONOSTEARATE; HEPTYL UNDECYLENATE; CETYL ALCOHOL; MEDIUM-CHAIN TRIGLYCERIDES; OLIVE OIL; TOCOPHEROL; PHENOXYETHANOL; ETHYLHEXYLGLYCERIN; HORSE CHESTNUT; CALENDULA OFFICINALIS FLOWER; CHAMAEMELUM NOBILE FLOWER

Earth's Care® Hemorrhoid Relief Cream

Drug Facts

ACTIVE INGREDIENT

Active ingredients | Purpose
Menthol USP 0.8% | Analgesic
Witch Hazel USP 10% | Astringent

Uses

- temporary relief of pain, itching, burning and discomfort associated with hemorrhoids
- may provide a cooling sensation
- can help distract from pain
- aids in protecting anorectal areas
- temporary relief of irritation

Warnings

For external use only

Allergy Alert

- Certain persons can develop allergic reactions to ingredients in this product

When using this product

- do not exceed the recommended daily dosage unless directed by a doctor
- do not put this product into the rectum by using fingers or any mechanical device or applicator

Stop use and ask a doctor

- if the symptom being treated does not subside or if redness, irritation, swelling, pain, or other symptoms develop or increase
- if bleeding occurs
- if condition worsens or does not improve within 7 days

PREGNANCY OR BREAST FEEDING

If pregnant or breast-feeding, ask a health professional before use.

Keep out of reach of children.

If swallowed, get medical help or contact a Poison Control Center right away.

Directions

Adults: When practical, cleanse the affected area with mild soap and warm water and rinse thoroughly. Gently dry by patting or drying with a tissue or a soft cloth before applying cream. When first opening the tube, remove cap and lift foil safety seal from tube. Apply externally to the affected area up to 6 times daily.

Children under 12 years of age: consult a doctor.

Inactive ingredients

aloe vera (Aloe barbadensis) gel, calendula (Calendula officinalis) flower extract, chamomile (Matricaria recutita) flower extract, caprylic/capric triglyceride, cetyl alcohol, cetyl hydroxyethylcellulose, ethylhexylglycerin, glycerin, glyceryl stearate, heptyl undecylenate, horse chestnut (Aesculus hippocastanum) seed extract, lanolin, olive (Olea europaea) oil, phenoxyethanol, polyglyceryl-3 dicitrate/stearate, sweet almond (Prunus amygdalus dulcis) oil, purified water, shea (Butyrospermum parkii) butter, tocopherols

Questions

1-888-602-6380

Distributed by:
Earth's Care Natural Products, Inc.
Long Beach, California 90805 USA

PRINCIPAL DISPLAY PANEL - 28 g Tube Box

No Vasoconstrictors

EARTH'S

CARE

PARABEN

FREE

Hemorrhoid

Relief Cream

Dual-Action Formula

Relieves external

discomfort

with Witch Hazel and

Menthol

1% FOR THE

PLANET

MEMBER

1OZ. (28g)